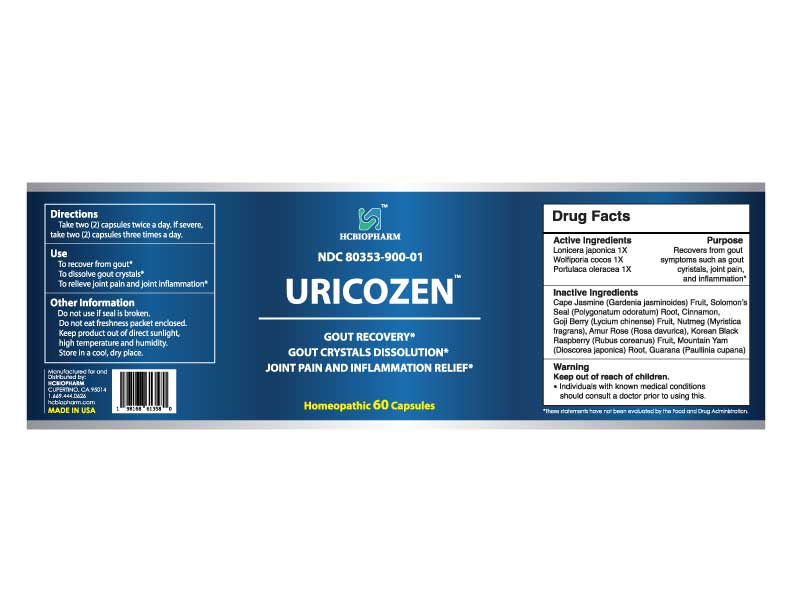 DRUG LABEL: URICOZEN
NDC: 80353-900 | Form: CAPSULE
Manufacturer: HCBIOPHARM
Category: homeopathic | Type: HUMAN OTC DRUG LABEL
Date: 20250103

ACTIVE INGREDIENTS: LONICERA JAPONICA FLOWER 1 [hp_X]/1 1; PORTULACA OLERACEA WHOLE 1 [hp_X]/1 1; WOLFIPORIA COCOS WHOLE 1 [hp_X]/1 1
INACTIVE INGREDIENTS: GARDENIA JASMINOIDES FRUIT; POLYGONATUM ODORATUM ROOT; PAULLINIA CUPANA WHOLE; CINNAMON; LYCIUM CHINENSE FRUIT; MYRISTICA FRAGRANS WHOLE; ROSA DAVURICA WHOLE; RUBUS COREANUS FRUIT; DIOSCOREA JAPONICA ROOT

ACTIVE INGREDIENT

Portulaca oleracea 1X

Lonicera japonica 1X

Wolfiporia cocos 1X

PURPOSE

Recovers from gout symptoms such as gout crystals, joint pain, and inflammation*

Keep out of reach of children

DOSAGE AND ADMINISTRATION

Take two (2) capsules twice a day. If severe, take two (2) capsules three times a day.

INDICATIONS AND USAGE

To recover from gout*

To dissolve gout crystals*

To relieve joint pain and joint inflammation*

INACTIVE INGREDIENT

Cape Jasmine (Gardenia jasminoides) Fruit, Solomon's Seal (Polygonatum odoratum) Root, Cinnamon, Goji Berry (Lycium chinense) Fruit, Nutmeg (Myristica fragrans), Amur Rose (Rosa davurica), Korean Black Raspberry (Rubus coreanus) Fruit, Mountain Yam (Dioscorea japonica) Root, Guarana (Paullinia cupana)

WARNINGS

Individuals with known medical conditions should consult a doctor prior to using this.

Do not use if seal is broken.

Do not eat freshness packet enclosed.

Keep out of direct sunlight, high temperature, and humidity.

Store in a cool, dry place.